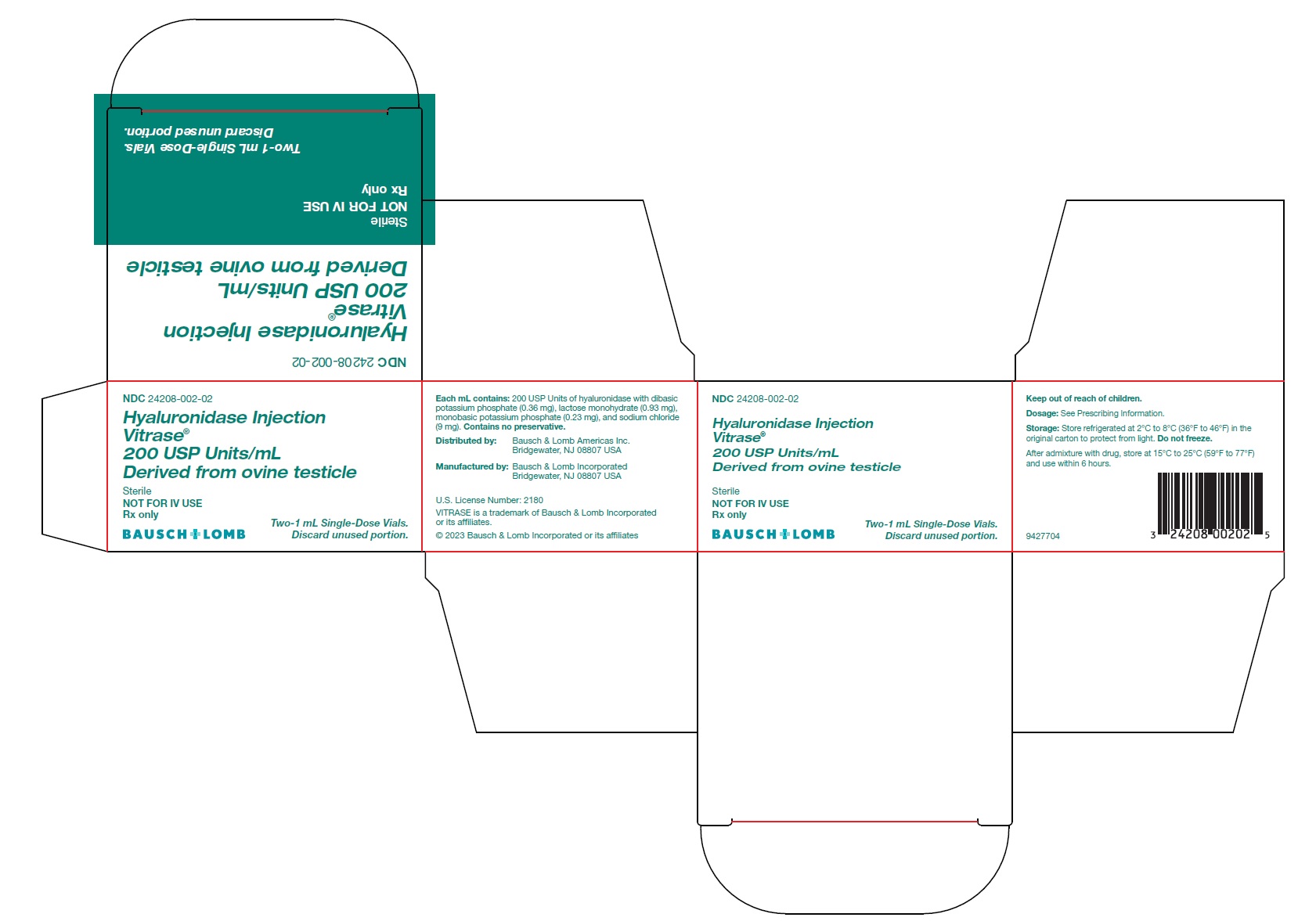 DRUG LABEL: VITRASE
NDC: 24208-002 | Form: INJECTION, SOLUTION
Manufacturer: Bausch & Lomb Incorporated
Category: prescription | Type: HUMAN PRESCRIPTION DRUG LABEL
Date: 20240531

ACTIVE INGREDIENTS: HYALURONIDASE (OVINE) 200 [USP'U]/1 mL
INACTIVE INGREDIENTS: MONOBASIC POTASSIUM PHOSPHATE 0.23 mg/1 mL; SODIUM CHLORIDE 9 mg/1 mL; LACTOSE, UNSPECIFIED FORM; DIBASIC POTASSIUM PHOSPHATE

HIGHLIGHTS OF PRESCRIBING INFORMATION

These highlights do not include all the information needed to use VITRASE safely and effectively. See full prescribing information for VITRASE.
VITRASE®(hyaluronidase injection), for infiltration use, for interstitial use, for intramuscular use, for intraocular use, for peribulbar use, for retrobulbar use, for soft tissue use, or for subcutaneous use
Initial U.S. Approval: 2004

1 INDICATIONS AND USAGE

VITRASE is an endoglycosidase indicated as an adjuvant:

- in subcutaneous fluid administration for achieving hydration. (1.1)
- for increasing the dispersion and absorption of other injected drugs. (1.2)
- for improving resorption of radiopaque agents, in subcutaneous urography. (1.3)

2 DOSAGE AND ADMINISTRATION

- Draw the desired amount of VITRASE into the syringe to obtain target hyaluronidase activity (USP Units) according to table. (2.1)
- Before adding VITRASE to a solution containing another drug check appropriate references regarding physical/chemical incompatibilities. (7)
- Subcutaneous Fluid Administration: Inject 200 Units of VITRASE prior to clysis. It will facilitate absorption of 1,000 mL or more of solution. The dosage of subcutaneous fluids administered depends upon the age, weight, clinical condition of the patient, and laboratory determinations. Rate and volume of subcutaneous fluid administration should not exceed those employed for intravenous infusion. (2.2, 8.4)
- Increasing absorption and dispersion of injected drugs: Add 50–300 Units (most typically 150 Units) of VITRASE to the injection solution. (2.3)
- Subcutaneous urography: With the patient prone, inject 75 Units of VITRASE subcutaneously over each scapula, followed by injection of the contrast medium at the same sites. (2.4)

3 DOSAGE FORMS AND STRENGTHS

Injection: 200 USP units/mL in a single-dose vial (3)

4 CONTRAINDICATIONS

Hypersensitivity (4)

5 WARNINGS AND PRECAUTIONS

- Spread of Localized Infection (5.1)
- Ocular Cornea Damage (5.2)
- Enzyme Inactivation with Intravenous Administration (5.3)

6 ADVERSE REACTIONS

Allergic and anaphylactic-like reactions have been reported, rarely. (6)

To report SUSPECTED ADVERSE REACTIONS, contact Bausch & Lomb Incorporated at 1-800-553-5340 or FDA at 1-800-FDA-1088 or www.fda.gov/medwatch.

7 DRUG INTERACTIONS

- Furosemide, benzodiazepines and phenytoin are incompatible with hyaluronidase. (7.1)
- Hyaluronidase should not be used to enhance the absorption and dispersion of dopamine and/or alpha agonist drugs. (7.2)
- Local anesthetics: Hyaluronidase hastens onset and shortens duration of effect, increases incidence of systemic reactions. (7.3)
- Large doses of salicylates, cortisone, adrenocorticotropic hormone (ACTH), estrogens or antihistamines: Concomitant use may require larger amounts of hyaluronidase for equivalent dispersing effect. (7.4)

8 USE IN SPECIFIC POPULATIONS

Pediatric Use: The dosage of subcutaneous fluids administered is dependent upon the age, weight, and clinical condition of the patient. For premature infants or during the neonatal period, the daily dosage should not exceed 25 mL/kg of body weight, and the rate of administration should not be greater than 2 mL per minute. Special care must be taken in pediatric patients to avoid overhydration by controlling the rate and total volume of the infusion (2.2, 8.4).

FULL PRESCRIBING INFORMATION

1 INDICATIONS AND USAGE

1.1 Subcutaneous Fluid Administration (Hypodermoclysis)

VITRASE®(hyaluronidase injection) is indicated as an adjuvant in subcutaneous fluid administration for achieving hydration.

1.2 Dispersion and Absorption of Injected Drugs

VITRASE is indicated as an adjuvant to increase the dispersion and absorption of other injected drugs.

1.3 Subcutaneous Urography

VITRASE is indicated as an adjuvant in subcutaneous urography for improving resorption of radiopaque agents.

2 DOSAGE AND ADMINISTRATION

2.1 Important Administration Instructions

Parenteral drug products should be inspected visually for particulate matter and discoloration prior to administration, whenever solution and container permit.

VITRASE should be administered as discussed below, since its effects relative to absorption and dispersion of other drugs are not produced when it is administered intravenously.

Draw the desired amount of VITRASE into the syringe to obtain the target Hyaluronidase Activity (USP Units) according to the table below.

Table 1. Amount of VITRASE Solution

Withdrawn Per Target

Hyaluronidase Activity

Target Hyaluronidase; Activity (USP Units) | Volume Withdrawn from Vial (mL)
50 Units | 0.25 mL
75 Units | 0.38 mL
150 Units | 0.75 mL
200 Units | 1.00 mL

After admixture with drug, store at 15°C to 25°C (59°F to 77°F) and use within 6 hours. Consult the Prescribing Information of other drugs for additional storage information.

2.2 Dosage for Subcutaneous Fluid Administration (Hypodermoclysis)

Insert needle with aseptic precautions. With tip free and movable between skin and muscle, begin clysis; fluid should start in readily without pain or lump. Then inject VITRASE into rubber tubing close to needle.

An alternate method is to inject VITRASE under skin prior to clysis. 200 Units will facilitate absorption of 1,000 mL or more of solution. As with all parenteral fluid therapy, observe effect closely, with same precautions for restoring fluid and electrolyte balance as in intravenous injections. The dose, the rate of injection, and the type of solution (saline, glucose, Ringer’s, etc.) must be adjusted carefully to the individual patient. When solutions devoid of inorganic electrolytes are given by hypodermoclysis, hypovolemia may occur. This may be prevented by using solutions containing adequate amounts of inorganic electrolytes and/or controlling the volume and speed of administration.

VITRASE may be added to small volumes of solution (up to 200 mL), such as small clysis for infants or solutions of drugs for subcutaneous injection. For infants and children less than 3 years old, the volume of a single clysis should be limited to 200 mL; and in premature infants or during the neonatal period, the daily dosage should not exceed 25 mL/kg of body weight; the rate of administration should not be greater than 2 mL per minute. For older patients, the rate and volume of administration should not exceed those employed for intravenous infusion.

2.3 Dosage for Absorption and Dispersion of Injected Drugs

Absorption and dispersion of other injected drugs may be enhanced by adding 50 Units to 300 Units, most typically 150 Units of VITRASE to the injection solution.

2.4 Dosage for Subcutaneous Urography

The subcutaneous route of administration of urographic contrast media is indicated when intravenous administration cannot be successfully accomplished, particularly in infants and small children. With the patient prone, 75 Units of VITRASE are injected subcutaneously over each scapula, followed by injection of the contrast medium at the same sites.

3 DOSAGE FORMS AND STRENGTHS

Injection: 200 USP Units/mL as a clear, colorless solution in a single-dose vial.

4 CONTRAINDICATIONS

VITRASE is contraindicated in patients with known hypersensitivity to hyaluronidase or any other ingredient in the formulation.

Discontinue VITRASE if sensitization occurs.

5 WARNINGS AND PRECAUTIONS

5.1 Spread of Localized Infection

Hyaluronidase should not be injected into or around infected or acutely inflamed area because of the danger of spreading to a localized infection. Hyaluronidase should not be used to reduce the swelling of bites or stings.

5.2 Ocular Cornea Damage

VITRASE should not be applied directly to the cornea.

5.3 Enzyme Inactivation with Intravenous Administration

VITRASE should not be used for intravenous injections because the enzyme is rapidly inactivated.

6 ADVERSE REACTIONS

The following adverse reactions have been identified during post-approval use of hyaluronidase products. Because these reactions are reported voluntarily from a population of uncertain size, it is not always possible to reliably estimate their frequency or establish a causal relationship to drug exposure. The most frequently reported adverse reactions have been local injection site reactions.

Hyaluronidase has been reported to enhance the adverse reactions associated with co-administered drug products. Edema has been reported most frequently in association with hypodermoclysis.

Allergic reactions (e.g., urticaria, angioedema) have been reported in less than 0.1% of patients receiving hyaluronidase. Anaphylactic-like reactions following retrobulbar block or intravenous injections have occurred, rarely.

7 DRUG INTERACTIONS

It is recommended that appropriate references be consulted regarding physical or chemical incompatibilities before adding VITRASE to a solution containing another drug.

7.1 Incompatibilities

Furosemide, benzodiazepines and phenytoin have been found to be incompatible with hyaluronidase.

7.2 Drug-Specific Precautions

Hyaluronidase should not be used to enhance the absorption and dispersion of dopamine and/or alpha agonist drugs.

When considering the administration of any other drug with hyaluronidase, it is recommended that appropriate references first be consulted to determine the usual precautions for the use of the other drug.

7.3 Local Anesthetic Agent

When hyaluronidase is added to a local anesthetic agent, it hastens the onset of analgesia and tends to reduce the swelling caused by local infiltration, but the wider spread of the local anesthetic solution increases its absorption; this shortens its duration of action and tends to increase the incidences of systemic reaction.

7.4 Salicylates, Cortisone, ACTH, Estrogens, Antihistamines

Patients receiving large doses of salicylates, cortisone, adrenocorticotropic hormone (ACTH), estrogens, or antihistamines may require larger amounts of hyaluronidase for equivalent dispersing effect, since these drugs apparently render tissues partly resistant to the action of hyaluronidase.

8 USE IN SPECIFIC POPULATIONS

8.1 Pregnancy

Risk Summary

Human studies of hyaluronidase as an aid to conception and as an aid to delivery have been conducted without reports of maternal or fetal harm. Non-human animal reproduction studies have not been conducted with VITRASE.

The estimated background risk of major birth defects and miscarriage for the indicated population is unknown. However, the background risk in the U.S. general population of major birth defects is 2 to 4%, and of miscarriage is 15 to 20%, of clinically recognized pregnancies.

Clinical Considerations

Hyaluronidase has been used as a component to aid the in vitrofertilization of human eggs. Administration of hyaluronidase during labor was reported to cause no complications; no increase in blood loss or differences in cervical trauma were observed.

8.2 Lactation

Risk Summary

There is no information regarding the presence of VITRASE in human milk, the effects on breastfed infants, or the effects on milk production to inform risk of VITRASE to an infant during lactation. The developmental and health benefits of breastfeeding should be considered, along with the mother’s clinical need for VITRASE, and any potential adverse effects on the breastfed infant from VITRASE.

8.4 Pediatric Use

The safety and effectiveness of VITRASE have been established in pediatric patients. Use of VITRASE in these patients is supported by evidence from adequate and well-controlled studies. Clinical hydration requirements for children can be achieved through administration of subcutaneous fluids facilitated with VITRASE.

The dosage of subcutaneous fluids administered is dependent upon the age, weight, and clinical condition of the patient as well as laboratory determinations. The potential for chemical or physical incompatibilities should be kept in mind [ see Drug Interactions (7)] .

The rate and volume of subcutaneous fluid administration should not exceed those employed for intravenous infusion. For premature infants or during the neonatal period, the daily dosage should not exceed 25 mL/kg of body weight, and the rate of administration should not be greater than 2 mL per minute.

During subcutaneous fluid administration, special care must be taken in pediatric patients to avoid overhydration by controlling the rate and total volume of the infusion [see Dosage and Administration (2.2)] .

8.5 Geriatric Use

No overall differences in safety or effectiveness have been observed between elderly and younger adult patients.

11 DESCRIPTION

Hyaluronidase is an endoglycosidase. VITRASE is a preparation of purified ovine testicular hyaluronidase, a protein enzyme. Hyaluronidase is composed of two major glycosylated forms, α and β. The exact chemical structure of this enzyme is unknown.

VITRASE (hyaluronidase injection) is supplied as a sterile, non-preserved, clear and colorless 1 mL solution in a single-dose vial for infiltration use, for interstitial use, for intramuscular use, for intraocular use, for peribulbar use, for retrobulbar use, for soft tissue use, or for subcutaneous use.

Each mL contains 200 USP units of hyaluronidase with dibasic potassium phosphate (0.36 mg), lactose monohydrate (0.93 mg), monobasic potassium phosphate (0.23 mg), and sodium chloride (9 mg). The solution has a pH of 6.4 to 7.2.

12 CLINICAL PHARMACOLOGY

12.1 Mechanism of Action

Hyaluronidase is a spreading or diffusing substance, which modifies the permeability of connective tissue through the hydrolysis of hyaluronic acid, a polysaccharide found in the intercellular ground substance of connective tissue, and of certain specialized tissues, such as the umbilical cord and vitreous humor. Hyaluronic acid is also present in the capsules of type A and C hemolytic streptococci. Hyaluronidase hydrolyzes hyaluronic acid by splitting the glucosaminidic bond between C1 of the glucosamine moiety and C4 of glucuronic acid. This temporarily decreases the viscosity of the cellular cement and promotes diffusion of injected fluids or of localized transudates or exudates, thus facilitating their absorption.

Hyaluronidase cleaves glycosidic bonds of hyaluronic acid and, to a variable degree, some other acid mucopolysaccharides of the connective tissue. The activity is measured in vitroby monitoring the decrease in the amount of an insoluble serum albumen-hyaluronic acid complex as the enzyme cleaves the hyaluronic acid component.

12.2 Pharmacodynamics

In the absence of hyaluronidase, material injected subcutaneously spreads very slowly. Hyaluronidase facilitates dispersion, provided local interstitial pressure is adequate to furnish the necessary mechanical impulse. Such an impulse is normally initiated by injected solutions. The rate and extent of dispersion and absorption is proportionate to the amount of hyaluronidase and the volume of solution.

The reconstitution of the dermal barrier removed by intradermal injection of hyaluronidase (over a range of 0.002 to 20 Units/mL) to adult humans indicated that at 24 hours the restoration of the barrier is incomplete and inversely related to the dosage of enzyme; at 48 hours the barrier is completely restored in all treated areas.

Results from an experimental study, in humans, on the influence of hyaluronidase in bone repair support the conclusion that this enzyme alone, in the usual clinical dosage, does not deter bone healing.

12.3 Pharmacokinetics

Knowledge of the mechanisms involved in the disappearance of injected hyaluronidase is limited. It is known, however, that the blood of a number of mammalian species including humans brings about the inactivation of hyaluronidase.

Studies have demonstrated that hyaluronidase is antigenic; repeated injections of relatively large amounts of this enzyme may result in the formation of neutralizing antibodies.

13 NONCLINICAL TOXICOLOGY

13.1 Carcinogenesis, Mutagenesis, Impairment of Fertility

Animal studies have not been conducted to determine whether hyaluronidase has carcinogenic or mutagenic potential.

Adequate fertility studies have not been conducted in animals, however, it has been reported that testicular degeneration may occur from the production of organ-specific antibodies against this enzyme following repeated injections.

16 HOW SUPPLIED/STORAGE AND HANDLING

16.1 How Supplied

VITRASE®(hyaluronidase injection) is supplied as 200 USP units/mL of sterile, non-preserved, clear and colorless solution in a single-dose, glass vial with a rubber stopper and aluminum seal. Discard unused portion.

- NDC 24208-002-02: 200 USP units/mL in a single-dose vial (NDC 24208-002-03) available in a carton containing 2 single-dose vials.

16.2 Storage and Handling

- Protect from light.
- Store unopened vial in refrigerator at 2°C to 8°C (36°F to 46°F).
- Do not freeze.

17 PATIENT COUNSELING INFORMATION

Reporting Adverse Reactions

Instruct patients to report adverse reactions including redness, swelling, itching, or pain at the injection site.

Interactions with Other Medications

Instruct patients to report if they are taking furosemide, benzodiazepines, phenytoin, dopamine and/or alpha agonists because these medications have been found to be incompatible with hyaluronidase.

Instruct patients to report if they are taking salicylates (e.g., aspirin), steroids (e.g., cortisone or estrogens) or antihistamines because larger amounts of hyaluronidase may be needed to achieve an equivalent dispersing effect.

Distributed by:
Bausch & Lomb Americas Inc.
Bridgewater, NJ 08807 USA

Manufactured by:
Bausch & Lomb Incorporated
Bridgewater, NJ 08807 USA
U.S. License Number: 2180
VITRASE is a trademark of Bausch & Lomb Incorporated or its affiliates.

© 2023 Bausch & Lomb Incorporated or its affiliates

9427904

PACKAGE/LABEL PRINCIPAL DISPLAY PANEL – Vitrase Carton Label

NDC24208-002-02

Hyaluronidase Injection Vitrase® 200 USP Units/mL Derived from ovine testicle Sterile NOT FOR IV USE Rx only

BAUSCH+LOMB

Two-1 ml Single-Dose Vials.
Discard unused portion.

9427704